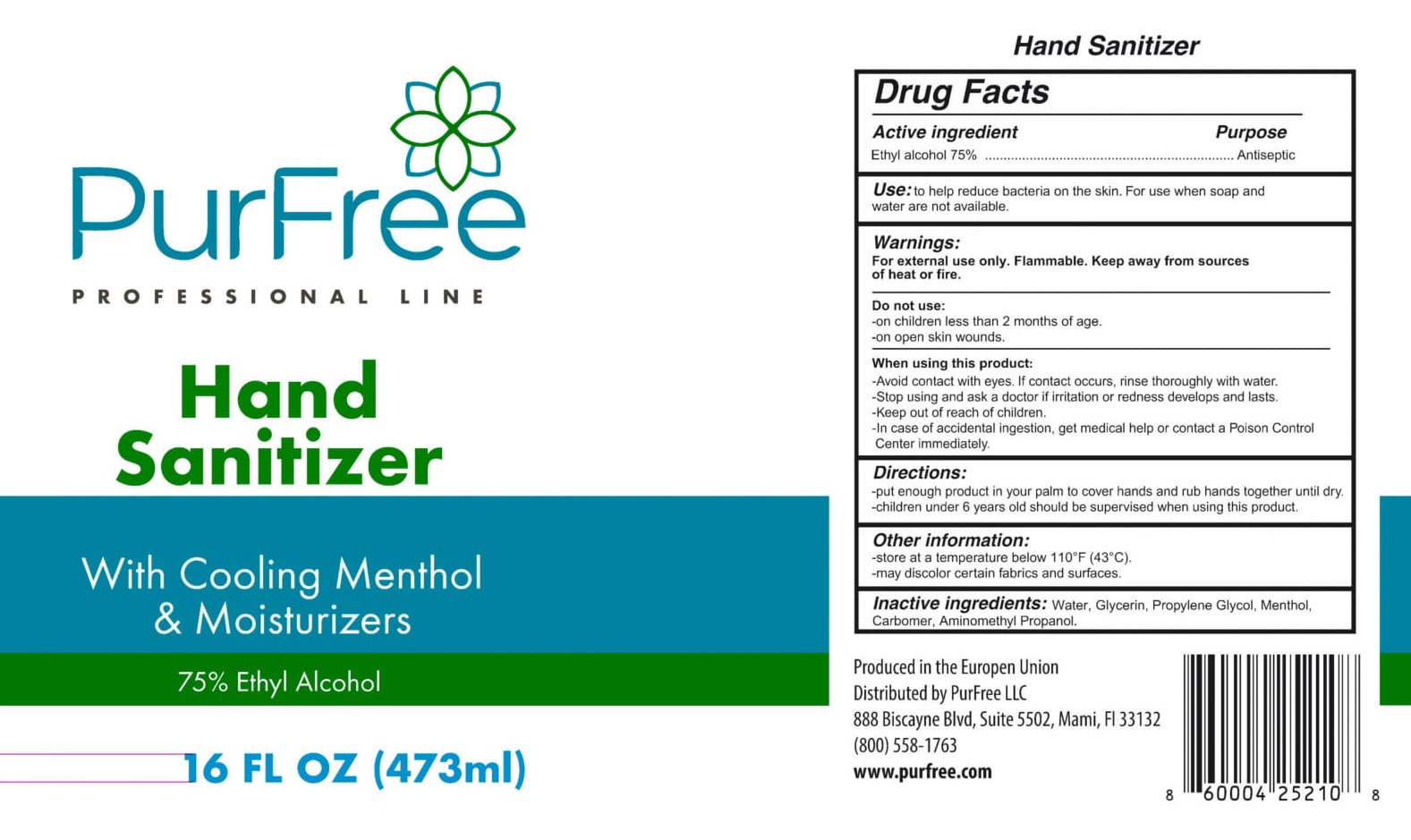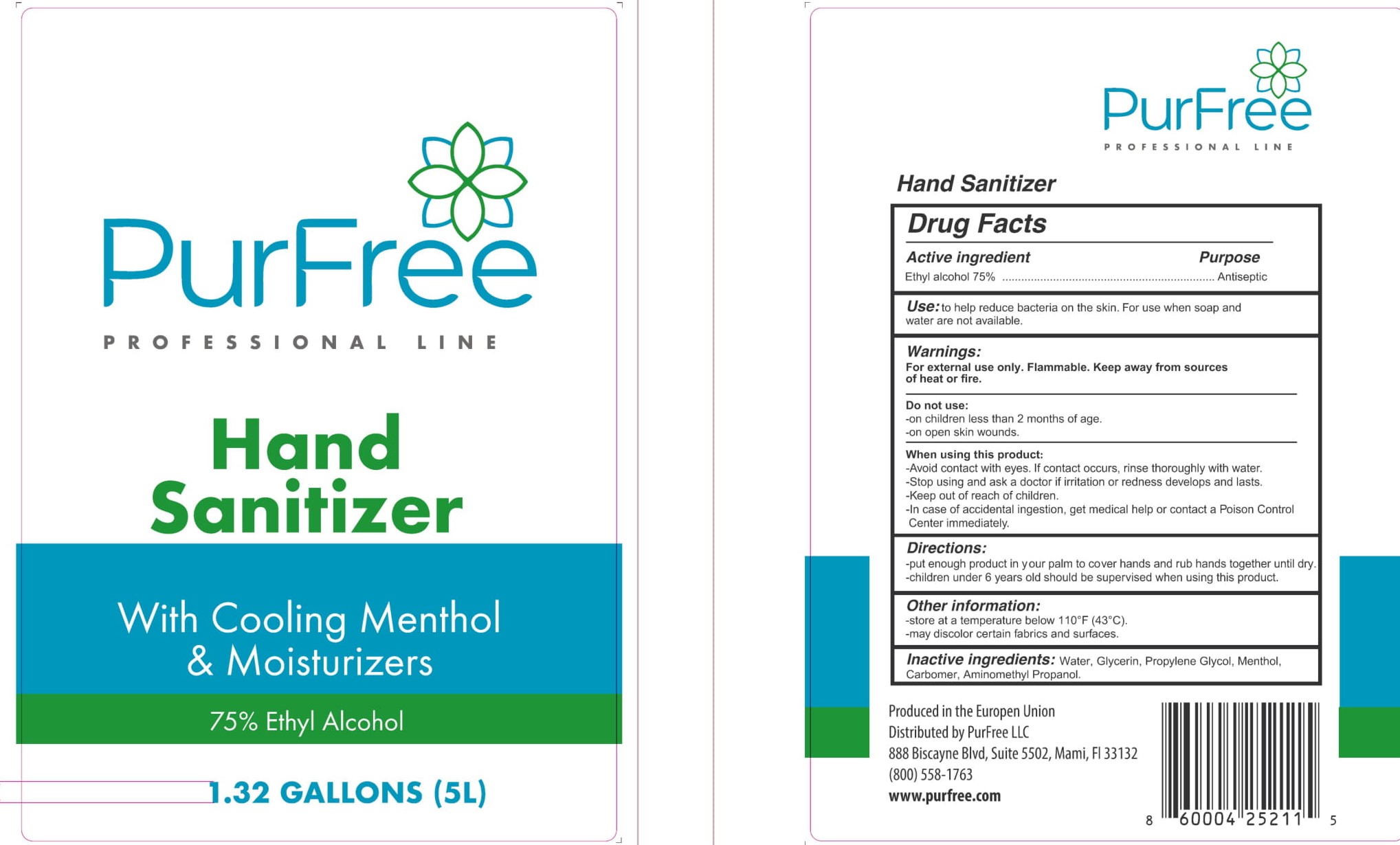 DRUG LABEL: PurFree Hand Sanitizer
NDC: 78717-001 | Form: GEL
Manufacturer: STERILCO SP Z O O
Category: otc | Type: HUMAN OTC DRUG LABEL
Date: 20210426

ACTIVE INGREDIENTS: ALCOHOL 75 mL/100 mL
INACTIVE INGREDIENTS: MENTHOL; DIPROPYLENE GLYCOL; WATER; GLYCERIN; CARBOMER HOMOPOLYMER, UNSPECIFIED TYPE; AMINOMETHYLPROPANOL

Hand Sanitiser PurFree

ACTIVE INGREDIENT

Alcohol 75% v/v. Purpose: Antiseptic

PURPOSE

Antiseptic, Hand Sanitizer

INDICATIONS AND USAGE

to help reduce bacteria on the skin. For use when soap and water are not available.

WARNINGS

For external use only. Flammable. Keep away from sources of heat or fire.

DO NOT USE

-on children less than 2 months of age.
-on open skin wounds.

WHEN USING

Avoid contact with eyes. If contact occurs, rinse thoroughly with water.

STOP USE

Stop using and ask a doctor if irritation or redness develops and lasts.

Keep out of reach of children.
In case of accidental ingestion, get medical help or contact a Poison Control Center immediately.

DOSAGE AND ADMINISTRATION

-put enough product in your palm to cover hands and rub hands together until dry.
-children under 6 years old should be supervised when using this product.

STORAGE AND HANDLING

-store at a temperature below 110°F (43°C).
-may discolor certain fabrics and surfaces.

INACTIVE INGREDIENT

water, Glycerin, Propylene Glycol, Menthol, Carbomer, Aminomethyl Propanol.